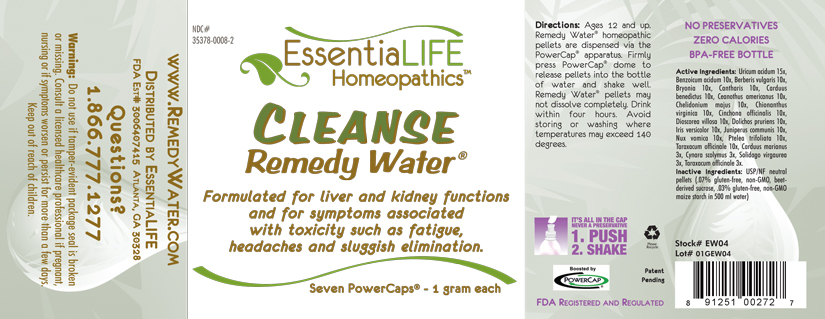 DRUG LABEL: Cleanse Remedy Water 
NDC: 35378-0008 | Form: PELLET
Manufacturer: Georgetown Health, LLC DBA EssentiaLife
Category: homeopathic | Type: HUMAN OTC DRUG LABEL
Date: 20120610

ACTIVE INGREDIENTS: Uric Acid 15 [hp_X]/1 mg; Benzoic Acid 10 [hp_X]/1 mg; Berberis Vulgaris Root Bark 10 [hp_X]/1 mg; Bryonia Alba Root 10 [hp_X]/1 mg; Lytta Vesicatoria 10 [hp_X]/1 mg; Cnicus Benedictus 10 [hp_X]/1 mg; Ceanothus Americanus Leaf 10 [hp_X]/1 mg; Chelidonium Majus 10 [hp_X]/1 mg; Chionanthus Virginicus Bark 10 [hp_X]/1 mg; Cinchona Officinalis Bark 10 [hp_X]/1 mg; Dioscorea Villosa Root 10 [hp_X]/1 mg; Mucuna Pruriens Fruit Trichome 10 [hp_X]/1 mg; Iris Versicolor Root 10 [hp_X]/1 mg; Strychnos Nux-vomica Seed 10 [hp_X]/1 mg; Ptelea Trifoliata Bark 10 [hp_X]/1 mg; Taraxacum Officinale 10 [hp_X]/1 mg; Silybum Marianum Seed 3 [hp_X]/1 mg; Cynara Scolymus Leaf 3 [hp_X]/1 mg; Solidago Virgaurea Flowering Top 3 [hp_X]/1 mg; Taraxacum Officinale 3 [hp_X]/1 mg; Juniperus Communis Whole 10 [hp_X]/1 mg
INACTIVE INGREDIENTS: Starch, Corn; Sucrose

Cleanse Remedy Water®

Active Ingredients

Uricum acidum | 15x
Benzoicum acidum | 10x
Berberis vulgaris | 10x
Bryonia | 10x
Cantharis | 10x
Carduus benedictus | 10x
Ceanothus americanus | 10x
Chelidonium majus | 10x
Chionanthus virginica | 10x
Cinchona officinalis | 10x
Dioscorea villosa | 10x
Dolichos pruriens | 10x
Iris versicolor | 10x
Juniperus communis | 10x
Nux vomica | 10x
Ptelea trifoliata | 10x
Taraxacum officinale | 10x
Carduus marianus | 3x
Cynara scolymus | 3x
Solidago virgaurea | 3x
Taraxacum officinale | 3x

Purpose

Formulated for liver and kidney functions and for symptoms associated with toxicity such as fatigue, headaches and sluggish elimination.

Uses

Formulated for liver and kidney functions and for symptoms associated with toxicity such as fatigue, headaches and sluggish elimination.

Warnings

Do not use if tamper-evident package seal is broken or missing. Consult a licensed healthcare professional if pregnant, nursing or if symptoms worsen or persist for more than a few days. Keep out of reach of children.

Directions

Ages 12 and up. Remedy Water® homepathic pellets are dispersed via the PowerCap® apparatus. Firmly press PowerCap® dome to release pellets into the bottle of water and shake well. Remedy Water® pellets may not dissolve completely. Drink within four hours. Avoid storing or washing where temperatures may exceed 140 degrees.

Inactive Ingredients

USP/NF neutral pellets (.07% gluten-free, non-GMO, beet-derived sucrose, .03% gluten-free, non-GMO maize starch in 500 ml water)

Other Information

Avoid storing in areas where temperatures may exceed 140 degrees.

Questions?

1.866.777.1277
www.RemedyWater.com

PRINCIPAL DISPLAY PANEL

NDC# 35378-0008-2

EssentiaLIFE Homeopathics™

CLEANSE Remedy Water®

Formulated for liver and kidney functions and for symptoms associated with toxicity such as fatigue, headaches and sluggish elimination.

Seven PowerCaps® - 1 gram each

Directions: Ages 12 and up. Remedy Water® homepathic pellets are dispersed via the PowerCap® apparatus. Firmly press PowerCap® dome to release pellets into the bottle of water and shake well. Remedy Water® pellets may not dissolve completely. Drink within four hours. Avoid storing or washing where temperatures may exceed 140 degrees.

IT'S ALL IN THE CAP
NEVER A PRESERVATIVE
1. PUSH
2. SHAKE

Please Recycle

Patent Pending

Boosted by PowerCap®

FDA Registered and Regulated

NO PRESERVATIVES
ZERO CALORIES
BPA-FREE BOTTLE

Active Ingredients: Uricum acidum 15x, Benzoicum acidum 10x, Berberis vulgaris 10x, Bryonia 10x, Cantharis 10x, Carduus benedictus 10x, Ceanothus americanus 10x, Chelidonium majus 10x, Chionanthus virginica 10x, Cinchona officinalis10x, Dioscorea villosa 10x, Dolichos pruriens 10x, Iris versicolor 10x, Juniperus communis 10x, Nux vomica 10x, Ptelea trioliata 10x, Taraxacum officinale10x, Carduus marianus 3x, Cynara scolymus 3x, Solidago virgaurea 3x, Taraxacum officinale 3x.

Inactive ingredients: USP/NF neutral pellets (.07% gluten-free, non-GMO, beet-derived sucrose, .03% gluten-free, non-GMO maize starch in 500 ml water)

Stock# EW04

Lot# 01GEW04

www.RemedyWater.com

Distributed by EssentiaLIFE

FDA Est# 3006407415 Atlanta, GA 30328

Questions?

1.866.777.1277

Warning: Do not use if tamper-evident package seal is broken or missing. Consult a licensed healthcare professional if pregnant, nursing or if symptoms worsen or persist for more than a few days. Keep out of reach of children.